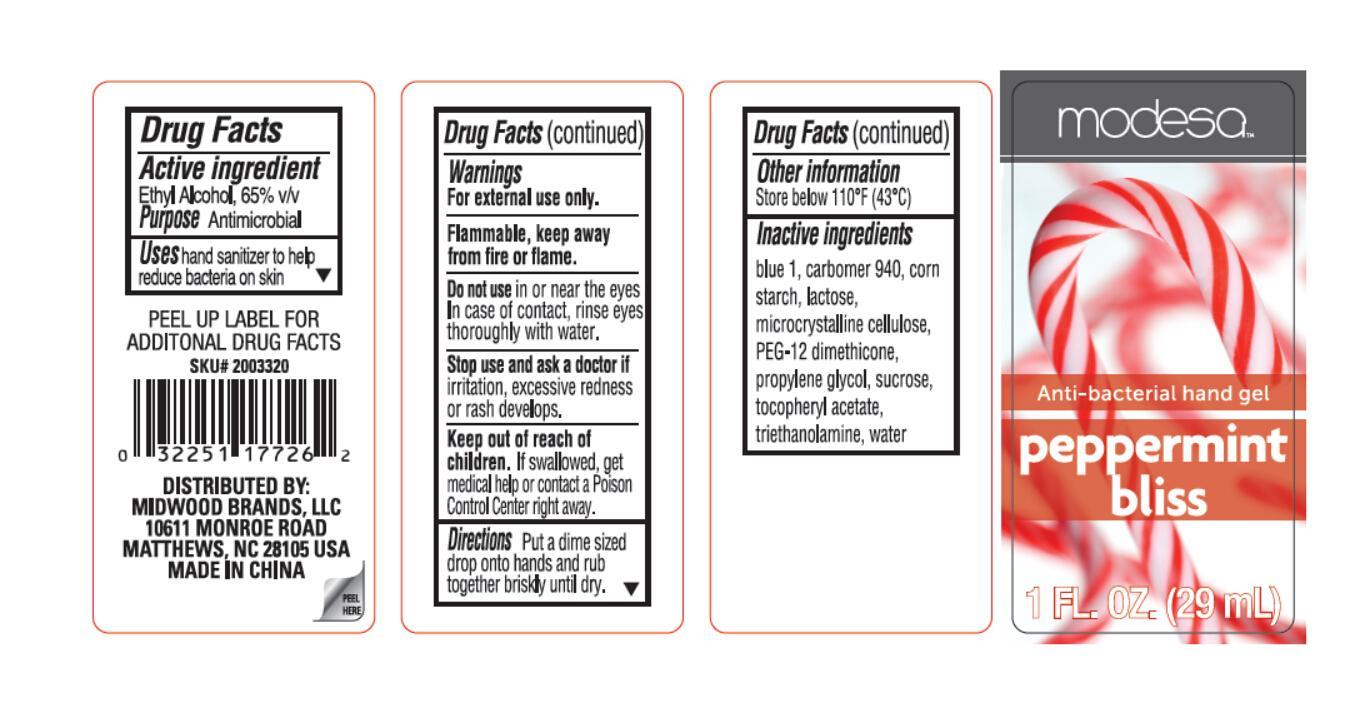 DRUG LABEL: Modesa
                
                
NDC: 58194-024 | Form: GEL
Manufacturer: Shanghai Weierya Daily Chemicals Factory
Category: otc | Type: HUMAN OTC DRUG LABEL
Date: 20150628

ACTIVE INGREDIENTS: ALCOHOL 65 mL/100 mL
INACTIVE INGREDIENTS: CARBOMER HOMOPOLYMER TYPE C (ALLYL PENTAERYTHRITOL CROSSLINKED); CELLULOSE, MICROCRYSTALLINE; LACTOSE; STARCH, CORN; SUCROSE; FD&C BLUE NO. 1; PROPYLENE GLYCOL; TROLAMINE; .ALPHA.-TOCOPHEROL ACETATE; PEG-12 DIMETHICONE (300 CST); WATER

Drug Facts

Inactive Ingredients

blue 1, carbomer 940, corn

starch, lactose,

microcrystalline cellulose,

PEG-12 dimethicone, propylene glycol,

sucrose, tocopheryl acetate,

triethanolamine,

water

Active Ingredient

Ethyl Alcohol 65 % v/v

Purpose Antimicrobial

Warnings

For external use only.

Keep out of reach of children. If swallowed,

get medical help or contact a Poison

Control Center right away.

Uses

hand sanitizer to help reduce bacteria on skin

DOSAGE AND ADMINISTRATION

Directions Put a dime sized drop onto hands

and rub together briskly until dry.

Do not use in or near the eyes.

In case of contact, rinse eyes

thoroughly with water.

Stop use and ask a doctor

if irritation, excessive redness or

rash develops.

OTHER SAFETY INFORMATION

Flammable. Keep away from

fire or flame.

Other Information

Store below 110 F (43 C)